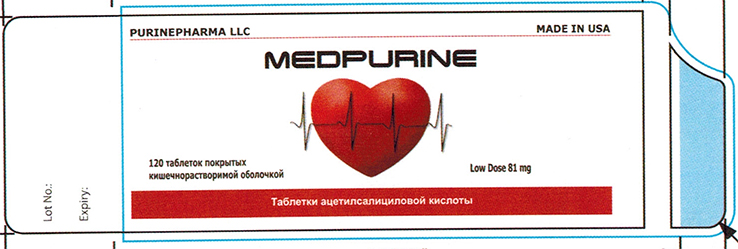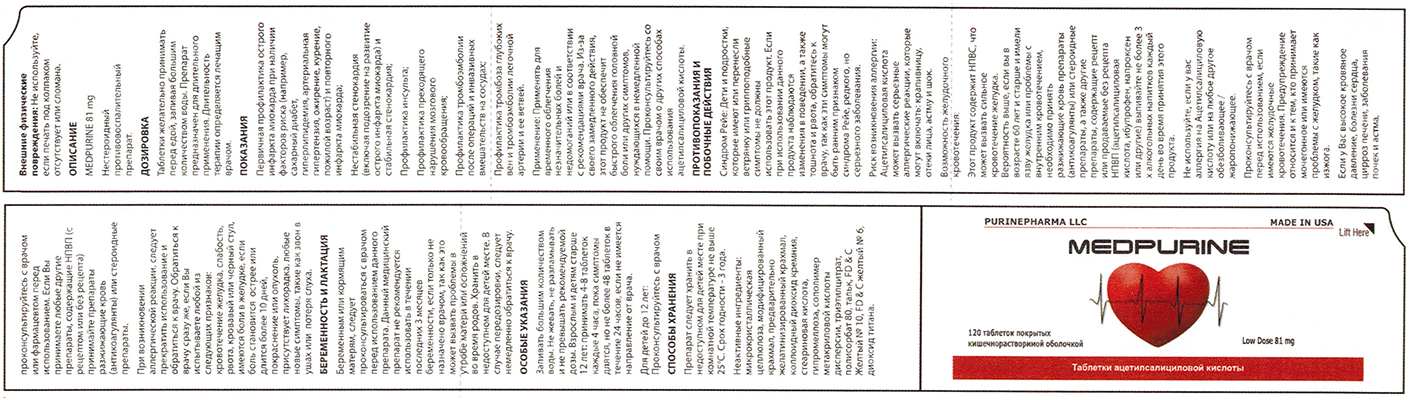 DRUG LABEL: MEDPURINE
NDC: 58599-016 | Form: TABLET
Manufacturer: PURINEPHARMA LLC
Category: otc | Type: HUMAN OTC DRUG LABEL
Date: 20150427

ACTIVE INGREDIENTS: ASPIRIN 81 mg/1 1
INACTIVE INGREDIENTS: CELLULOSE, MICROCRYSTALLINE; STARCH, CORN; SILICON DIOXIDE; STEARIC ACID; HYPROMELLOSES; METHACRYLIC ACID; GLATIRAMER ACETATE; CLOSPIRAZINE HYDROCHLORIDE; TRIETHYL CITRATE; POLYSORBATE 80; TALC; D&C YELLOW NO. 10; FD&C YELLOW NO. 6; TITANIUM DIOXIDE

MEDPURINE

Active Ingredient (in each tablet): Aspirin 81 mg (NSAID) [nonsteroidal anti-inflammatory drug]

Purpose: Pain reliever

INDICATIONS AND USAGE

Uses For the temporary relief of minor aches and pains or as recommended by your doctor. Because of its delayed action, this product will not provide fast relief of headaches or other symptoms needing immediate relief. Ask your doctor about other uses of aspirin.

Warnings

Reye's syndrome: Children and teenagers who have or are recovering from chicken pox or flu-like symptoms should not use this product. When using this product, if changes in behavior with nausea and vomiting occur, consult a doctor because these symptoms could be an early sign of Reye's syndrome, a rare but serious illness.

Allergy alert: Aspirin may cause a severe allergic reaction which may include: hives facial swelling asthma (wheezing) shock

Stomach bleeding warning: This product contains an NSAID, which may cause severe stomach bleeding. The chance is higher if you are age 60 or older have had stomach ulcers or bleeding problems take a blood thinning (anticoagulant) or steroid drug take other drugs containing prescription or nonprescription NSAIDs (aspirin, ibuprofen, naproxen, or others) have 3 or more alcoholic drinks every day while using this product Take more or for a longer time than directed

Do not use if you are allergic to aspirin or any other pain reliever / fever reducer.

Ask a doctor before use if the stomach bleeding warning
you are taking a diuretic
you have a history of stomach problems, such as heartburn
You have high blood pressure, heart disease, liver cirrhosis, kidney disease
You have asthma

Ask a doctor or pharmacist before use if you are taking any other drugs containing an NSAID (prescription or nonprescription)
taking a blood thinning (anticoagulant) or steroid drug
taking a prescription drug for diabetes, gout or arthritis

Stop use and ask a doctor if an allergic reaction occurs. Seek medical right away. you experience any of the following signs of stomach bleeding, feel faint, vomit blood, have bloody or black stools, have stomach pain that does not get better, pain gets worse or lasts more than 10 days, redness or swelling is present, fever gets worse or lasts more than 3 days, any new symptoms occur, ringing in the ears or a loss of hearing occurs

PREGNANCY OR BREAST FEEDING

If pregnant or breast-feeding, ask a health professional before use. It is especially important not to use aspirin during the last 3 months of pregnancy unless definitely directed to do so by a doctor because it may cause problems in the unborn child or complications during delivery.

Keep out of reach of children. In case of overdose, get medical help or contact a Poison Control Center right away.

DOSAGE AND ADMINISTRATION

Directions drink a full glass of water with each dose. Swallow whole. Do not chew or crush. Do not exceed recommended dose.
Adults and children 12 years and older: Take 4-8 tablets every 4 hours while symptoms last, but not more than 48 tablets in 24 hours unless directed by a doctor.
Children under 12: Ask a doctor.

Other information save carton for full directions and warnings. Store at room temperature

INACTIVE INGREDIENT

Inactive ingredients: Microcrystalline Cellulose, Modified Starch, Pregelatinized Starch, Colloidal Silicon Dioxide, Stearic Acid, Hypromellose, Methacrylic Acid Copolymer Dispersion, Triethyl Citrate, Polysorbate 80, Talc, FD&C Yellow #10, FD&C Yellow #6, Titanium Dioxide.

HOW SUPPLIED

NDC 58599-016-30: 120 Count in a Bottle